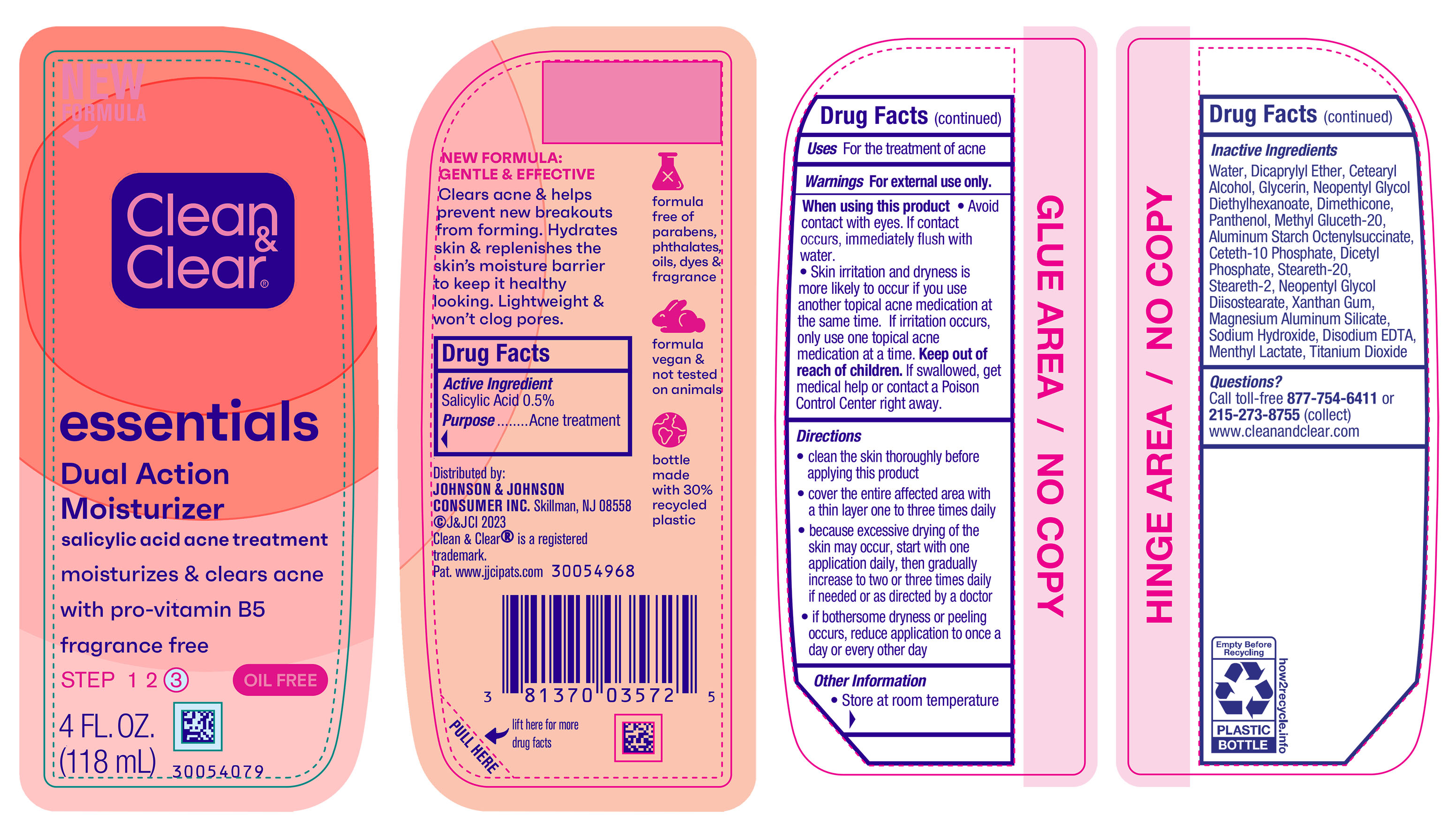 DRUG LABEL: Clean and Clear Essentials Dual Action Moisturizer
NDC: 69968-0803 | Form: LOTION
Manufacturer: Kenvue Brands LLC
Category: otc | Type: HUMAN OTC DRUG LABEL
Date: 20241106

ACTIVE INGREDIENTS: SALICYLIC ACID 5 mg/1 mL
INACTIVE INGREDIENTS: WATER; DICAPRYLYL ETHER; CETOSTEARYL ALCOHOL; GLYCERIN; NEOPENTYL GLYCOL DIETHYLHEXANOATE; DIMETHICONE; METHYL GLUCETH-20; MENTHYL LACTATE, (-)-; ALUMINUM STARCH OCTENYLSUCCINATE; CETETH-10 PHOSPHATE; DIHEXADECYL PHOSPHATE; PANTHENOL; STEARETH-20; STEARETH-2; NEOPENTYL GLYCOL DIISOSTEARATE; SODIUM HYDROXIDE; XANTHAN GUM; MAGNESIUM ALUMINUM SILICATE; EDETATE DISODIUM ANHYDROUS; TITANIUM DIOXIDE

Clean and Clear Essentials Dual Action Moisturizer

Drug Facts

Active ingredient

Salicylic Acid 0.5%

Purpose

Acne treatment

Use

For the treatment of acne

Warnings

For external use only.

When using this product

▪ Avoid contact with eyes. If contact occurs, immediately flush with water.

▪ Skin irritation and dryness is more likely to occur if you use another topical acne medication at the same time. If irritation occurs, only use one topical acne medication at a time.

Keep out of reach of children. If swallowed, get medical help or contact a Poison Control Center right away.

Directions

- clean the skin thoroughly before applying this product
- cover the entire affected area with a thin layer one to three times daily
- because excessive drying of the skin may occur, start with one application daily, then gradually increase to two or three times daily if needed or as directed by a doctor
- if bothersome dryness or peeling occurs, reduce application to once a day or every other day

Other information

- Store at room temperature

Inactive ingredients

Water, Dicaprylyl Ether, Cetearyl Alcohol, Glycerin, Neopentyl Glycol Diethylhexanoate, Dimethicone, Panthenol, Methyl Gluceth-20, Aluminum Starch Octenylsuccinate, Ceteth-10 Phosphate, Dicetyl Phosphate, Steareth-20, Steareth-2, Neopentyl Glycol Diisostearate, Xanthan Gum, Magnessium Aluminum Silicate, Sodium Hydroxide, Disodium EDTA, Menthyl Lactate, Titanium Dioxide

Questions?

Call toll-free 877-754-6411 or 215-273-8755 (collect) www.cleanandclear.com

Distributed by:
JOHNSON & JOHNSON
CONSUMER INC.
Skillman, NJ 08558

PRINCIPAL DISPLAY PANEL - 118 mL Bottle Label

NEW

FORMULA

Clean

&

Clear®

essentials

Dual Action

Moisturizer

salicylic acid acne treatment

moisturizes & clears acne

with pro-vitamin B5

fragrance free

STEP 1 2 ③

OIL FREE

4 FL. OZ.

(118 mL)